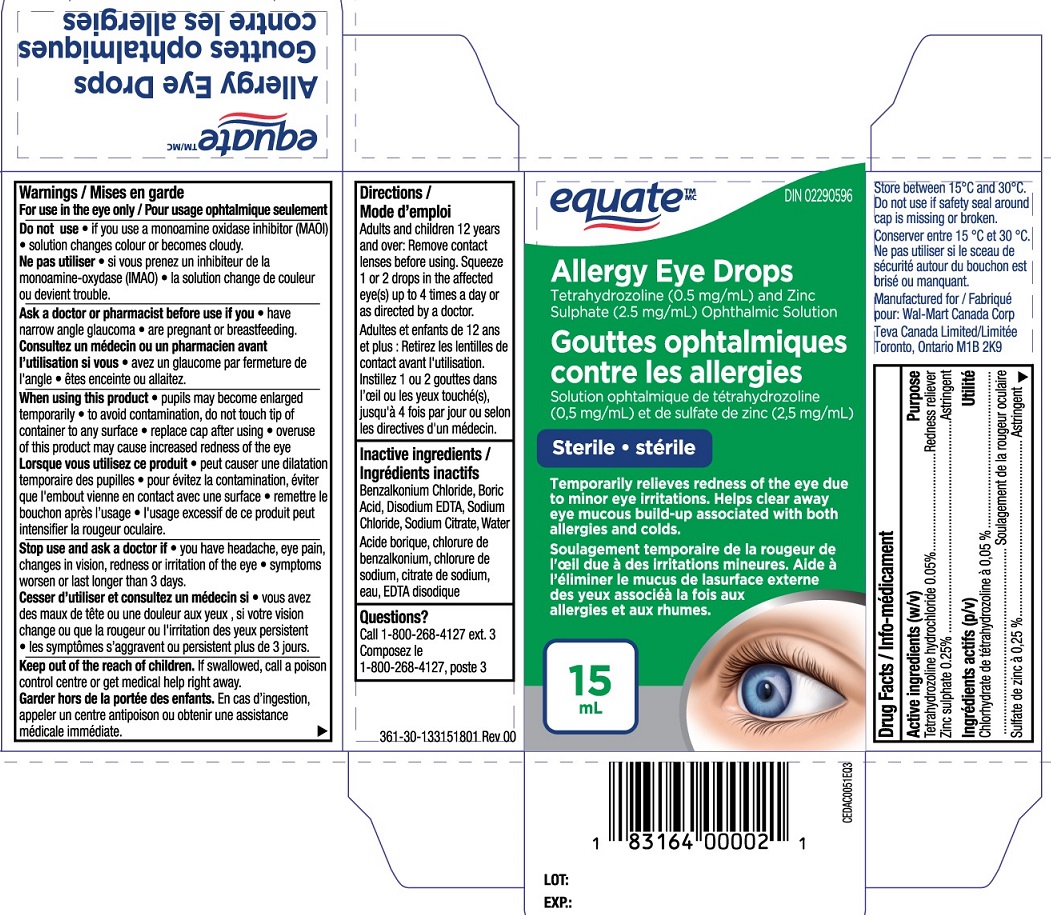 DRUG LABEL: Equate Allergy Eye Drops
NDC: 55651-040 | Form: SOLUTION
Manufacturer: KC Pharmaceuticals, Inc.
Category: otc | Type: HUMAN OTC DRUG LABEL
Date: 20251231

ACTIVE INGREDIENTS: TETRAHYDROZOLINE HYDROCHLORIDE 0.05 g/100 mL; ZINC SULFATE 0.25 g/100 mL
INACTIVE INGREDIENTS: BENZALKONIUM CHLORIDE; WATER; EDETATE DISODIUM; SODIUM CHLORIDE; SODIUM CITRATE; BORIC ACID

Equate Allergy Eye Drops 15 mL MFR